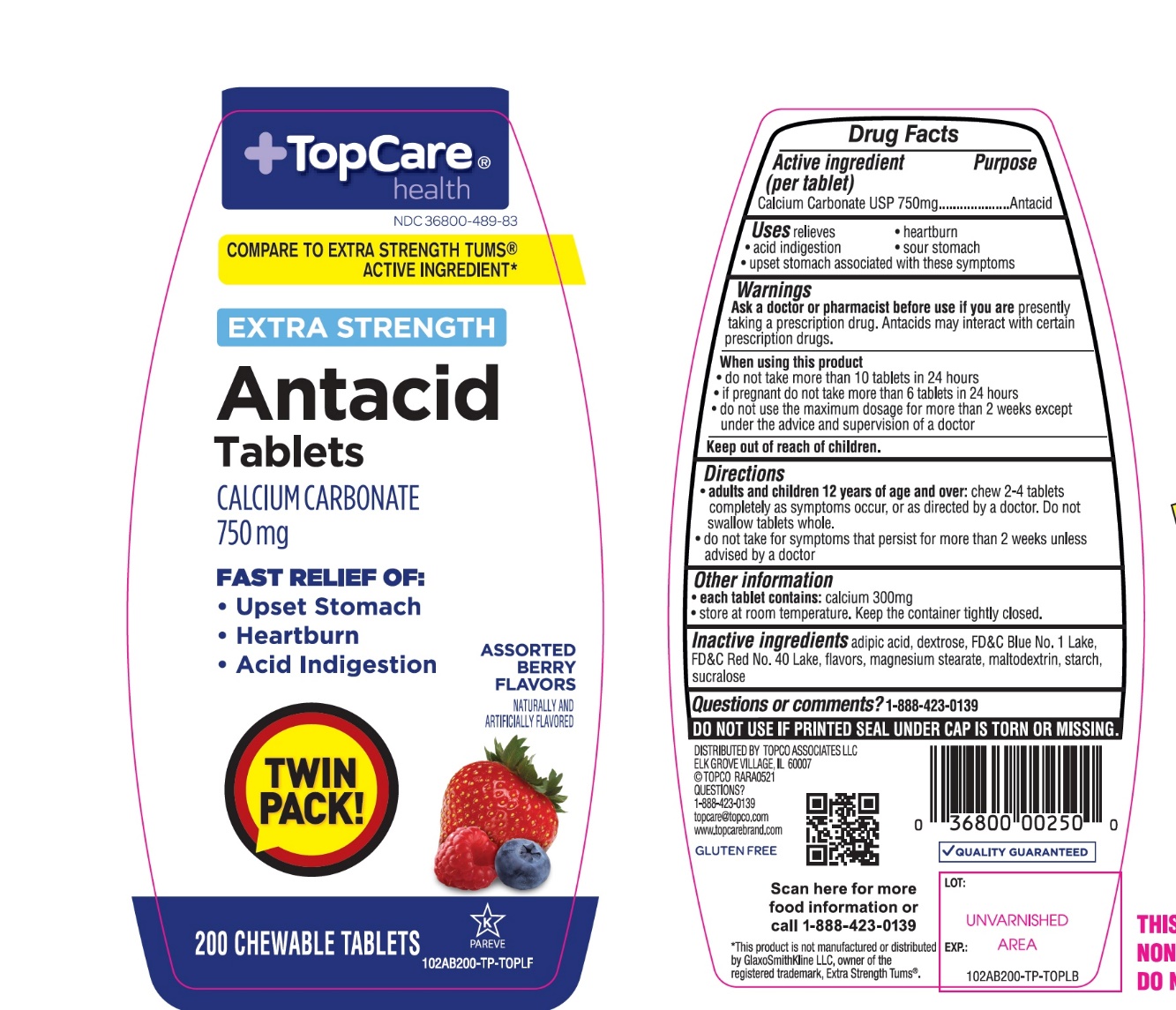 DRUG LABEL: Topcare Antacid Calcium

NDC: 36800-489 | Form: TABLET, CHEWABLE
Manufacturer: Topco Associates LLC
Category: otc | Type: HUMAN OTC DRUG LABEL
Date: 20251108

ACTIVE INGREDIENTS: CALCIUM CARBONATE 750 mg/1 1
INACTIVE INGREDIENTS: ADIPIC ACID; DEXTROSE, UNSPECIFIED FORM; FD&C BLUE NO. 1; FD&C RED NO. 40; MAGNESIUM STEARATE; MALTODEXTRIN; STARCH, CORN; SUCRALOSE

Topco Associates LLC. Antacid Calcium Drug Facts

Active ingredient (per tablet)

Calcium Carbonate USP 750mg

Purpose

Antacid

Uses

relieves

- heartburn
- acid indigestion
- sour stomach
- upset stomach associated with these symptoms

Warnings

Ask a doctor or pharmacist before use if you are

presently taking a prescription drug. Antacids may interact with certain prescription drugs.

When using this product

- do not take more than 10 tablets in 24 hours
- if pregnant do not take more than 6 tablets in 24 hours
- do not use the maximum dosage for more than 2 weeks except under the advice and supervision of a doctor

Directions

- adults and children 12 years of age and over:chew 2-4 tablets as symptoms occur, or as directed by a doctor
- do not take for symptoms that persist for more than 2 weeks unless advised by a doctor

Other information

- each tablet contains: elemental calcium 300mg
- store at room temperature. Keep the container tightly closed.

Inactive ingredients

adipic acid, dextrose, FD&C blue #1 aluminum lake, FD&C red #40 aluminum lake, flavors, magnesium stearate, maltodextrin, starch, sucralose.

Questions?

1-888-423-0139

Safety sealed: Do not use if printed seal under cap is torn or missing.

Principal Display Panel

NDC#38600-489-83

+TopCare®health™

COMPARE TO EXTRA STRENGTH TUMS® ACTIVE INGREDIENT*

EXTRA STRENGTH

Antacid Tablets

CALCIUM CARBONATE 750 mg

FAST RELIEF OF:

- Upset Stomach
- Heartburn
- Acid indigestion

ASSORTED BERRY FLAVORS

TWIN PACK!

200 CHEWABLE TABLETS

GLUTEN FREE

ASSORTED BERRY FLAVORS

200 CHEWABLE TABLETS

K PAREVE

QUALITY GUARANTEED

For questions or comments, please call

1-888-423-0139.

DISTRIBUTED BY TOPCO ASSOCIATES LLC

ELK GROVE VILLAGE, IL 60007

© TOPCO RARA0918

QUESTIONS? 1-888-423-0139

topcare@topco.comwww.topcarebrand.com

Visit here for more information: http://topbrnds.com/48ZS0KN

*This product is not manufactured or distributed by GlaxoSmithKline LLC, owner of the registered trademark, Extra Strength Tums®.